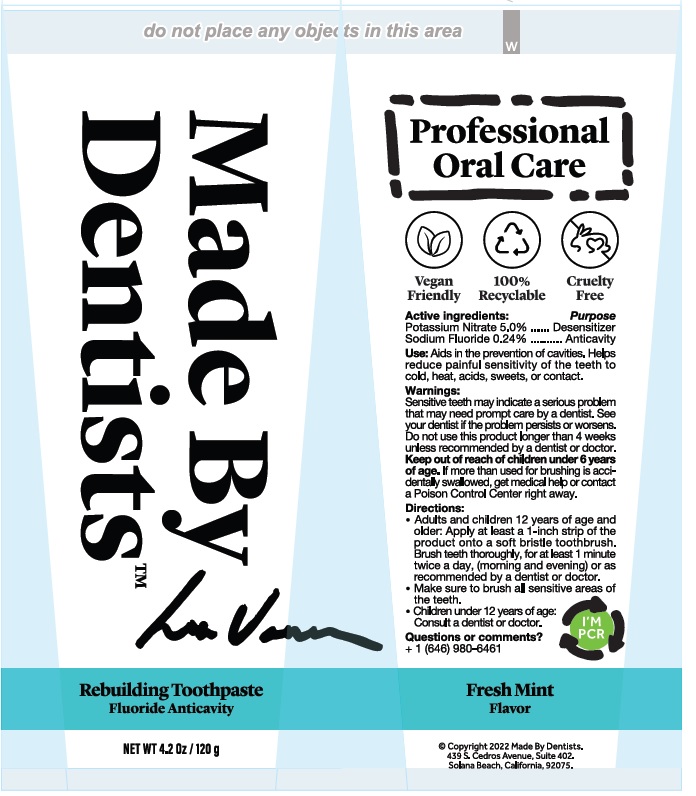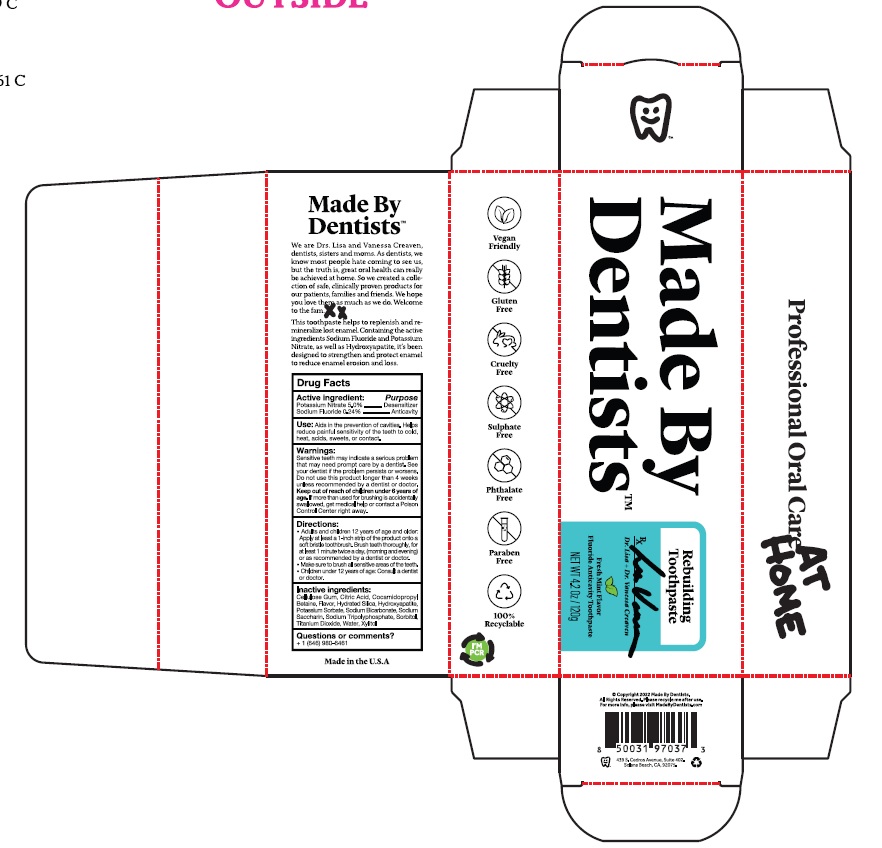 DRUG LABEL: Made By Dentists, Inc.  Rebuilding
NDC: 75065-019 | Form: PASTE
Manufacturer: Made By Dentists, Inc.
Category: otc | Type: HUMAN OTC DRUG LABEL
Date: 20251208

ACTIVE INGREDIENTS: POTASSIUM NITRATE 5 g/100 g; SODIUM FLUORIDE 0.24 g/100 g
INACTIVE INGREDIENTS: CARBOXYMETHYLCELLULOSE SODIUM, UNSPECIFIED; CITRIC ACID MONOHYDRATE; COCAMIDOPROPYL BETAINE; HYDRATED SILICA; TRIBASIC CALCIUM PHOSPHATE; POTASSIUM SORBATE; SODIUM BICARBONATE; SACCHARIN SODIUM; SODIUM TRIPOLYPHOSPHATE ANHYDROUS; SORBITOL; TITANIUM DIOXIDE; WATER; XYLITOL

Made By Dentists Rebuilding Toothpaste

Drug Facts

Active ingredient:

Potassium Nitrate 5.0%

Sodium Fluoride 0.24%

Purpose

Potassium Nitrate .... Desensitizer

Sodium Fluoride ....... Anticavity

INDICATIONS AND USAGE

Use: Aids in the prevention of cavities. Helps
Reduce painful sensitivity of teeth to cold,
heat, acids, sweets, or contact.

Warnings:

Sensitive teeth may indicate a serious problem
that may need prompt care by a dentist. See
your dentist if the problem persists or worsens.
Do not use this product longer than 4 weeks
unless recommended by a dentist or doctor.

Keep out of reach of children under 6 years of age.If
more than used for brushing is accidentally swallowed, get
medical help or contact a Poison Control Center right away.

Directions:
• Adults and children 12 years of age and older:
Apply at least a 1-inch strip of the product onto a
soft bristle toothbrush. Brush teeth thoroughly for
at least 1 minute twice a day, (morning and evening)
or as recommended by a dentist or doctor.
• Make sure to brush all sensitive areas of the teeth.
• Children under 12 years of age: Consult a dentist
or doctor.

Inactive Ingredients:
Cellulose Gum, Citric Acid, Cocamidopropyl
Betaine, Flavor, Hydrated Silica, Hydroxyapatite,
Potassium Sorbate, Sodium Bicarbonate, Sodium
Saccharin, Sodium Tripolyphosphate, Sorbitol,
Titanium Dioxide, Water, Xylitol

Questions? +1 (646) 980-6461

Rebuilding Toothpaste Product Labeling

Rebuilding Toothpaste

Made By Dentists™

Fresh Mint Flavor

NET WT 4.2 Oz / 120g

MADE IN THE USA

@Copyright: 2022 Made By Dentists

439 S. Cedros Avenue, Suite 402.

Solana Beach, CA, 92075

Carton

Tube

res